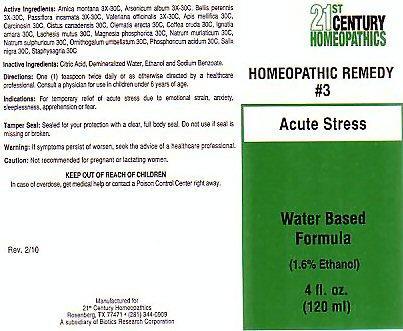 DRUG LABEL: CENTURY 21 ACUTE STRESS
NDC: 63972-003 | Form: LIQUID
Manufacturer: 21st Century Homeopathics, Inc
Category: homeopathic | Type: HUMAN OTC DRUG LABEL
Date: 20100101

ACTIVE INGREDIENTS: ARNICA MONTANA 30 [hp_C]/5 mL; ARSENIC TRIOXIDE 30 [hp_C]/5 mL; BELLIS PERENNIS 30 [hp_C]/5 mL; PASSIFLORA INCARNATA FLOWERING TOP 30 [hp_C]/5 mL; VALERIAN 30 [hp_C]/5 mL; APIS MELLIFERA 30 [hp_C]/5 mL; HUMAN BREAST TUMOR CELL 30 [hp_C]/5 mL; HELIANTHEMUM CANADENSE 30 [hp_C]/5 mL; CLEMATIS RECTA FLOWERING TOP 30 [hp_C]/5 mL; ARABICA COFFEE BEAN 30 [hp_C]/5 mL; STRYCHNOS IGNATII SEED 30 [hp_C]/5 mL; LACHESIS MUTA VENOM 30 [hp_C]/5 mL; MAGNESIUM PHOSPHATE, DIBASIC TRIHYDRATE 30 [hp_C]/5 mL; SODIUM CHLORIDE 30 [hp_C]/5 mL; SODIUM SULFATE 30 [hp_C]/5 mL; ORNITHOGALUM UMBELLATUM 30 [hp_C]/5 mL; PHOSPHORIC ACID 30 [hp_C]/5 mL; SALIX NIGRA BARK 30 [hp_C]/5 mL; DELPHINIUM STAPHISAGRIA SEED 30 [hp_C]/5 mL
INACTIVE INGREDIENTS: CITRIC ACID MONOHYDRATE; WATER; ALCOHOL; SODIUM BENZOATE

Active Ingredients

Active Ingredients: Arnica montana 3X-30C, Arsenicum album 3X-30C, Bellis perennis 3X-30C, Passiflora incarnata 3X-30C, Valeriana officinalis 3X-30C, Apis mellifica 30C, Carcinosin 30C, Cistus canadensis 30C, Clematis erecta 30C, Coffea cruda 30C, Ignatia amara 30C, Lachesis mutus 30C, Magnesia phosphorica 30C, Natrum muriaticum 30C, Natrum sulphuricum 30C, Ornithogalum umbellatum 30C, Phosphoricum acidum 30C, Salix nigra 30C, Staphysagria 30C.

Inactive Ingredients

Inactive Ingredients: Citric acid, demineralized water, Ethanol and Sodium benzoate.

Directions For Use

Directions: One (1) teaspoon twice daily or as otherwise directed by a healthcare professional. Consult a physician for use in children under 6 years of age.

Indications

Indications: For temporary relief of acute stress due to emotional strain, anxiety, sleeplessness, apprehension or fear.

Keep Out Of Reach Of Children

In case of overdose, get medical help or contact a Poison Control Center right away.

Purpose

Acute Stress

Warnings

Warning:If symptoms persist or worsen, seek the advice of a healthcare professional.
Caution: Not recommended for pregnant or lactating women.

PRODUCT LABEL

21st CENTURY HOMEOPATHICS
HOMEOPATHIC REMEDY # 3 Acute Stress
Water based Formula (1.6% Ethanol) 4 fl. oz. (120ml)
Tamper Seal: Sealed for your protection with a clear, full body seal. Do not use if seal is missing or broken.
Rev. 2/10 Manufactured for 21st Century Homeopathics Rosenburg, Tx 77471 (281) 344-0909 A subsidiary of Biotics Research Corporation